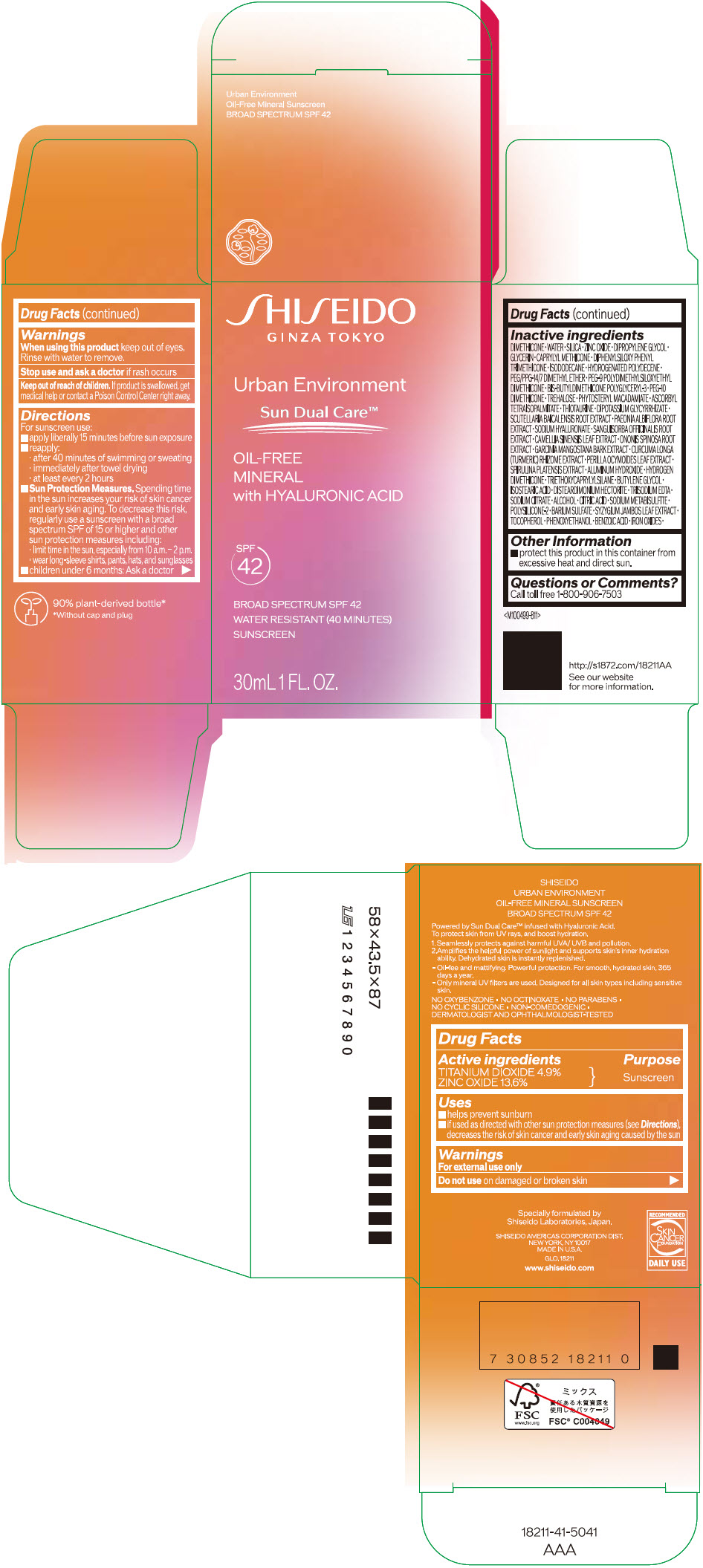 DRUG LABEL: SHISEIDO URBAN ENVIRONMENT oil-free MINERAL SUNSCREEN SPF 42
NDC: 58411-672 | Form: EMULSION
Manufacturer: SHISEIDO AMERICAS CORPORATION
Category: otc | Type: HUMAN OTC DRUG LABEL
Date: 20260204

ACTIVE INGREDIENTS: TITANIUM DIOXIDE 1.8 g/30 mL; ZINC OXIDE 5 g/30 mL
INACTIVE INGREDIENTS: DIMETHICONE; WATER; SILICON DIOXIDE; DIPROPYLENE GLYCOL; GLYCERIN; CAPRYLYL TRISILOXANE; DIPHENYLSILOXY PHENYL TRIMETHICONE; ISODODECANE; HYDROGENATED POLYDECENE TYPE I; PEG/PPG-14/7 DIMETHYL ETHER; PEG-9 POLYDIMETHYLSILOXYETHYL DIMETHICONE; PEG-10 DIMETHICONE (600 CST); TREHALOSE; PHYTOSTERYL MACADAMIATE; ASCORBYL TETRAISOPALMITATE; THIOTAURINE; GLYCYRRHIZINATE DIPOTASSIUM; SCUTELLARIA BAICALENSIS ROOT; PAEONIA LACTIFLORA ROOT; HYALURONATE SODIUM; SANGUISORBA OFFICINALIS ROOT; GREEN TEA LEAF; ONONIS SPINOSA ROOT; GARCINIA MANGOSTANA BARK; TURMERIC; PERILLA FRUTESCENS LEAF; ALUMINUM HYDROXIDE; HYDROGEN DIMETHICONE (13 CST); TRIETHOXYCAPRYLYLSILANE; BUTYLENE GLYCOL; ISOSTEARIC ACID; DISTEARDIMONIUM HECTORITE; EDETATE TRISODIUM; SODIUM CITRATE, UNSPECIFIED FORM; ALCOHOL; CITRIC ACID MONOHYDRATE; SODIUM METABISULFITE; BARIUM SULFATE; SYZYGIUM JAMBOS LEAF; TOCOPHEROL; PHENOXYETHANOL; BENZOIC ACID; FERRIC OXIDE RED; FERRIC OXIDE YELLOW

SHISEIDO URBAN ENVIRONMENT OIL-FREE MINERAL SUNSCREEN SPF 42

Drug Facts

ACTIVE INGREDIENT

Active ingredients | Purpose
TITANIUM DIOXIDE 4.9% | Sunscreen
ZINC OXIDE 13.6% | Sunscreen

Uses

- helps prevent sunburn
- if used as directed with other sun protection measures (see Directions), decreases the risk of skin cancer and early skin aging caused by the sun

Warnings

For external use only

Do not useon damaged or broken skin

WHEN USING

When using this productkeep out of eyes. Rinse with water to remove.

Stop use and ask a doctorif rash occurs.

Keep out of reach of children.If product is swallowed, get medical help or contact a Poison Control Center right away.

Directions

For sunscreen use:

- apply liberally 15 minutes before sun exposure
- reapply:
  - after 40 minutes of swimming or sweating
  - immediately after towel drying
  - at least every 2 hours
- Sun Protection Measures. Spending time in the sun increases your risk of skin cancer and early skin aging. To decrease this risk, regularly use a sunscreen with a broad spectrum SPF of 15 or higher and other sun protection measures including:
  - limit time in the sun, especially from 10 a.m. – 2 p.m.
  - wear long-sleeve shirts, pants, hats, and sunglasses
- children under 6 months: Ask a doctor

Inactive Ingredients

DIMETHICONE • WATER • SILICA • ZINC OXIDE • DIPROPYLENE GLYCOL • GLYCERIN • CAPRYLYL METHICONE • DIPHENYLSILOXY PHENYL TRIMETHICONE • ISODODECANE • HYDROGENATED POLYDECENE • PEG/PPG-14/7 DIMETHYL ETHER • PEG-9 POLYDIMETHYLSILOXYETHYL DIMETHICONE • BIS-BUTYLDIMETHICONE POLYGLYCERYL-3 • PEG-10 DIMETHICONE • TREHALOSE • PHYTOSTERYL MACADAMIATE • ASCORBYL TETRAISOPALMITATE • THIOTAURINE • DIPOTASSIUM GLYCYRRHIZATE • SCUTELLARIA BAICALENSIS ROOT EXTRACT • PAEONIA ALBIFLORA ROOT EXTRACT • SODIUM HYALURONATE • SANGUISORBA OFFICINALIS ROOT EXTRACT • CAMELLIA SINENSIS LEAF EXTRACT • ONONIS SPINOSA ROOT EXTRACT • GARCINIA MANGOSTANA BARK EXTRACT • CURCUMA LONGA (TURMERIC) RHIZOME EXTRACT • PERILLA OCYMOIDES LEAF EXTRACT • SPIRULINA PLATENSIS EXTRACT • ALUMINUM HYDROXIDE • HYDROGEN DIMETHICONE • TRIETHOXYCAPRYLYLSILANE • BUTYLENE GLYCOL • ISOSTEARIC ACID • DISTEARDIMONIUM HECTORITE • TRISODIUM EDTA • SODIUM CITRATE • ALCOHOL • CITRIC ACID • SODIUM METABISULFITE • POLYSILICONE-2 • BARIUM SULFATE • SYZYGIUM JAMBOS LEAF EXTRACT • TOCOPHEROL • PHENOXYETHANOL • BENZOIC ACID • IRON OXIDES •

Other information

- protect this product in this container from excessive heat and direct sun.

Questions or comments?

Call toll free 1-800-906-7503

PRINCIPAL DISPLAY PANEL - 30 mL Bottle Carton

SHISEIDO
GINZA TOKYO

Urban Environment

Sun Dual Care™

OIL-FREE
MINERAL
with HYALURONIC ACID

SPF
42

BROAD SPECTRUM SPF 42
WATER RESISTANT (40 MINUTES)
SUNSCREEN

30mL 1 FL. OZ.